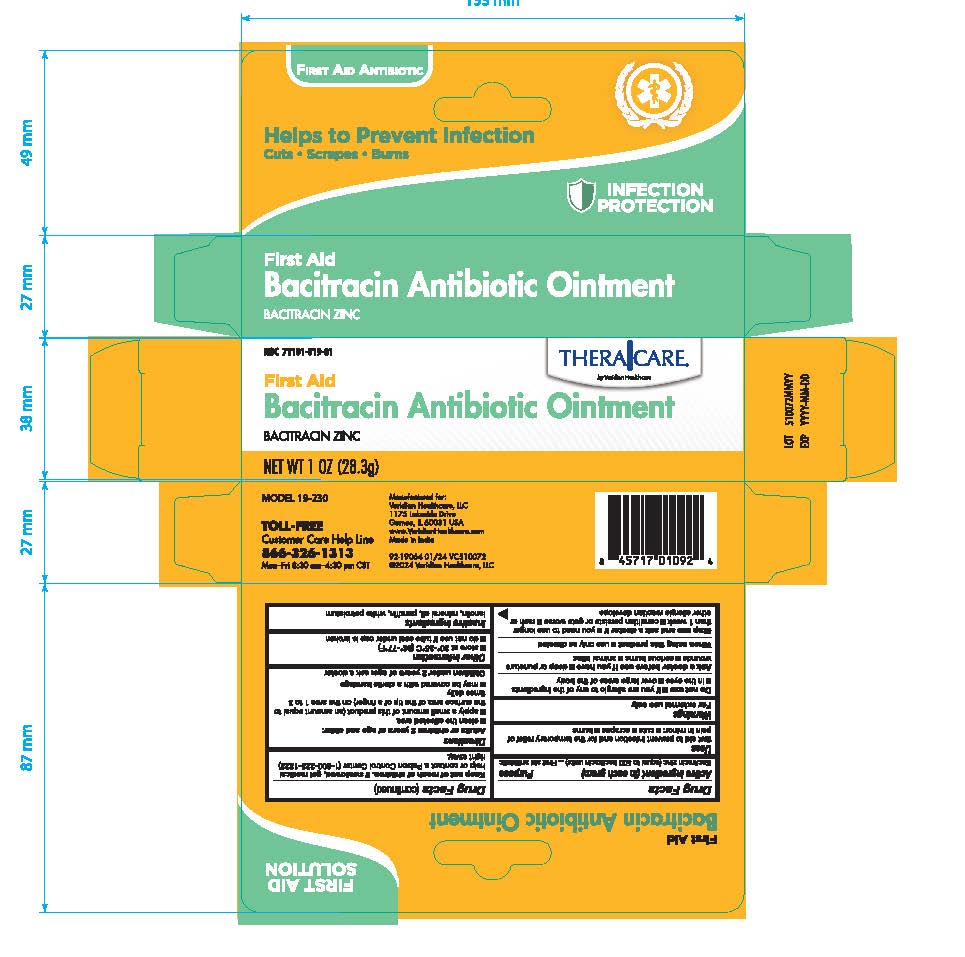 DRUG LABEL: TheraCare Bacitracin Zinc
NDC: 71101-019 | Form: OINTMENT
Manufacturer: Veridian Healthcare
Category: otc | Type: HUMAN OTC DRUG LABEL
Date: 20260129

ACTIVE INGREDIENTS: BACITRACIN ZINC 500 [USP'U]/1 g
INACTIVE INGREDIENTS: PARAFFIN; LANOLIN; WHITE PETROLATUM; MINERAL OIL

TheraCare Bacitracin Zinc

Active Ingredient

Bacitracin Zinc (500 units in each gram)

Purpose

First Aid Antibiotic

Uses

first aid to help prevent infection in minor cuts, scrapes, and burns

Warnings

For external use only

Do not use

- if you are allergic to any of the ingredients
- in the eyes
- over large areas of the body

Ask a doctor before use if you have

deep or puncture wounds, serious burns, animal bites

Stop use and ask a doctor if

- you need to use longer than 1 week
- the condition persists or gets worse
- rash or other allergic reaction develops

Keep out of reach of children

If swallowed, get medical help or contact a Poison Control Center (1-800-222-1222) right away.

When using this product

use as directed

Directions

adults or children 2 years of age and older:

- Clean the affected area.
- Apply a small amount of this product (an amount equal to the surface area of the tip of a finger) on the area 1 to 3 times daily.
- May be covered with a sterile bandage.

children under 2 years of age:ask a doctor

Other Information

- store at room temperature 20-25C (68-78F)
- do not use if tube seal under cap is broken

Inactive Ingredients

lanolin, mineral Oil, Paraffin, White Petrolatum

Questions and comments?

866-326-1313